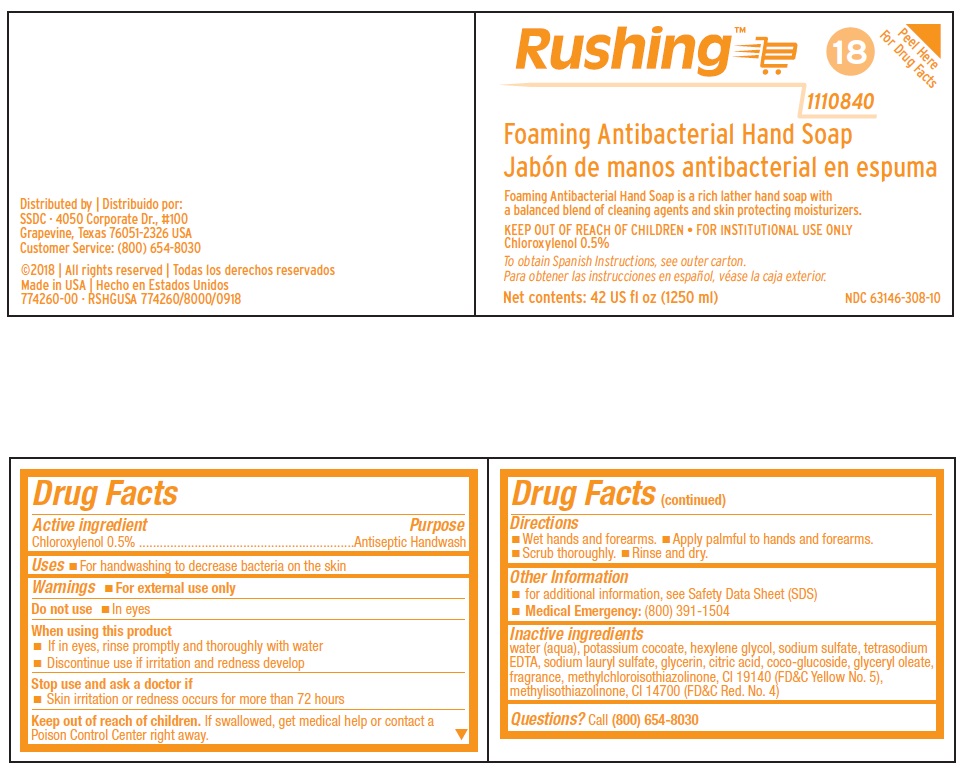 DRUG LABEL: RUSHING FOAMING ANTIBACTERIAL HANDSOAP
NDC: 47593-682 | Form: SOLUTION
Manufacturer: Ecolab Inc.
Category: otc | Type: HUMAN OTC DRUG LABEL
Date: 20251230

ACTIVE INGREDIENTS: CHLOROXYLENOL 5 mg/1 mL
INACTIVE INGREDIENTS: WATER; POTASSIUM COCOATE; HEXYLENE GLYCOL; SODIUM SULFATE; EDETATE SODIUM; SODIUM LAURYL SULFATE; GLYCERIN; ANHYDROUS CITRIC ACID; COCO-GLUCOSIDE; GLYCERYL OLEATE; METHYLCHLOROISOTHIAZOLINONE; FD&C YELLOW NO. 5; METHYLISOTHIAZOLINONE; FD&C RED NO. 4

Drug Facts

Active ingredient

Chloroxylenol 0.5%

Purpose

Antiseptic Handwash

Uses

- For handwashing to decrease bacteria on the skin.

Warnings

- For external use only

Do not use

- In eyes

When using this product

- If in eyes, rinse promptly and thoroughly with water
- Discontinue use if irritation and redness develop

Stop use and ask a doctor if

- Skin irritation or redness occurs for more than 72 hours

Keep out of reach of children. If swallowed, get medical help or contact a Poison Control Center right away.

Directions

- Wet hands and forearms • Apply palmful to hands and forearms.
- Scrub thoroughly • Rinse and dry.

Other Information

- for additional information, see Safety Data Sheet (SDS)
- Medical Emergency: (800) 391-1504

INACTIVE INGREDIENT

Inactive ingredients: water (aqua), potassium cocoate, hexylene glycol, sodium sulfate, tetrasodium EDTA, sodium lauryl sulfate, glycerin, citric acid, coco-glucoside, glyceryl oleate, fragrance, methychloroisothiazolinone, CI 19140 (FD&C Yellow No. 5), methylisothiazolinone, CI 14700 (FDC Red No. 4)

Questions? Call (800) 654-8030

Principal display panel and representative label

Rushing

1110840

Foaming Antibacterial Hand Soap

Foaming Antibacterial Hand Soap is a rich lather hand soap with

a balanced blend of cleaning agents and skin protecting moisturizers.

KEEP OUT OF REACH OF CHILDREN • FOR INSTITUTIONAL USE ONLY

Chloroxylenol 0.5%

To obtain Spanish Instructions, see outer carton.

Net contents: 42 US fl oz (1250 ml) NDC 63146-308-10

Distributed by | Distribuido por:

SSDC · 4050 Corporate Dr., #100

Grapevine, Texas 76051-2326 USA

Customer Service: (800) 654-8030

©2018 | All rights reserved | Todas los derechos reservados

Made in USA | Hecho en Estados Unidos

774260-00 · RSHGUSA 774260/8000/0918